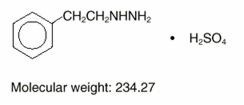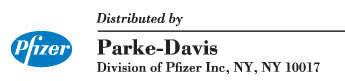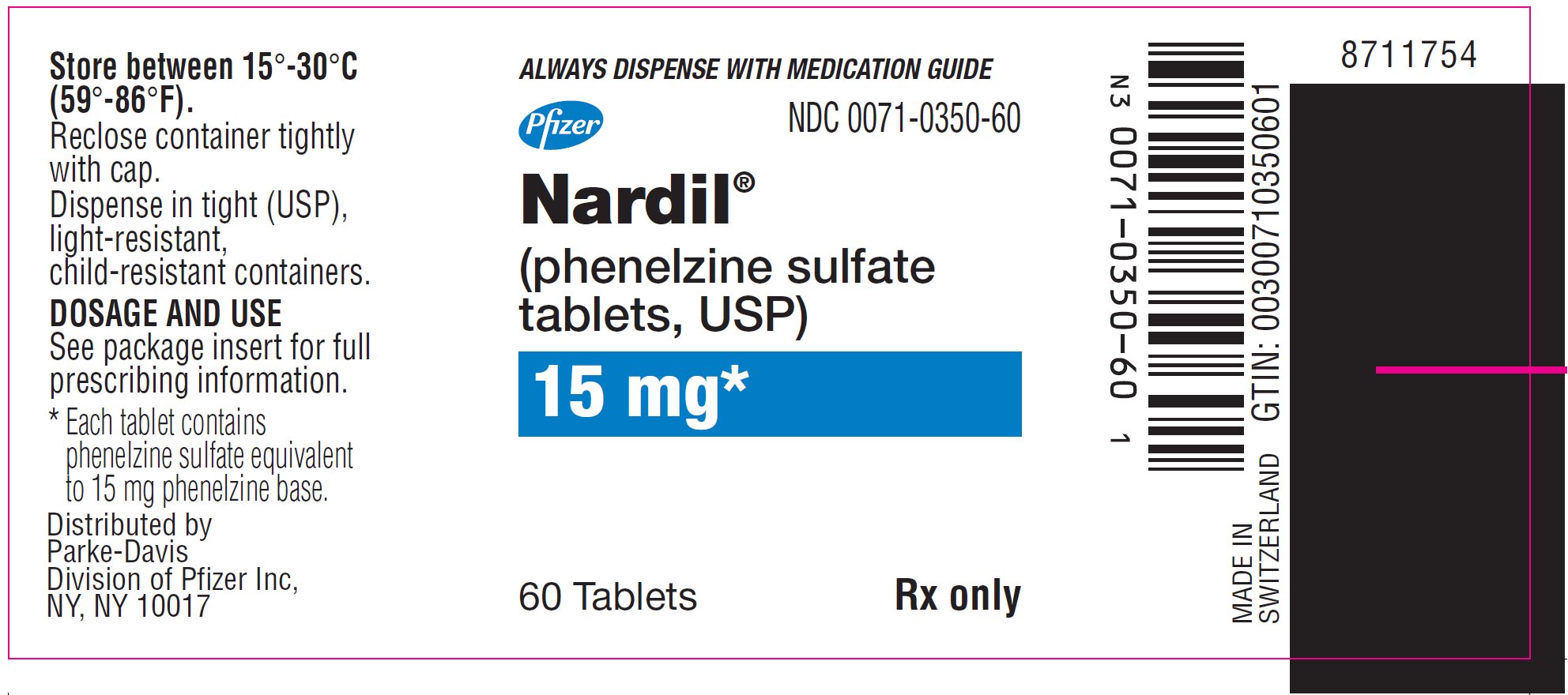 DRUG LABEL: Nardil
NDC: 0071-0350 | Form: TABLET, FILM COATED
Manufacturer: Parke-Davis Div of Pfizer Inc
Category: prescription | Type: HUMAN PRESCRIPTION DRUG LABEL
Date: 20250606

ACTIVE INGREDIENTS: PHENELZINE SULFATE 15 mg/1 1
INACTIVE INGREDIENTS: MANNITOL; CROSCARMELLOSE SODIUM; POVIDONE, UNSPECIFIED; EDETATE DISODIUM; MAGNESIUM STEARATE; ISOPROPYL ALCOHOL; WATER

NARDIL®
(Phenelzine Sulfate Tablets, USP)

Suicidality and Antidepressant Drugs

Antidepressants increased the risk compared to placebo of suicidal thinking and behavior (suicidality) in children, adolescents, and young adults in short-term studies of major depressive disorder (MDD) and other psychiatric disorders. Anyone considering the use of Nardil or any other antidepressant in a child, adolescent, or young adult must balance this risk with the clinical need. Short-term studies did not show an increase in the risk of suicidality with antidepressants compared to placebo in adults beyond age 24; there was a reduction in risk with antidepressants compared to placebo in adults aged 65 and older. Depression and certain other psychiatric disorders are themselves associated with increases in the risk of suicide. Patients of all ages who are started on antidepressant therapy should be monitored appropriately and observed closely for clinical worsening, suicidality, or unusual changes in behavior. Families and caregivers should be advised of the need for close observation and communication with the prescriber. Nardil is not approved for use in pediatric patients. (See Warnings: Clinical Worsening and Suicide Risk, Precautions: Information for Patients, and Precautions: Pediatric Use)

DESCRIPTION

NARDIL® (phenelzine sulfate) is a potent inhibitor of monoamine oxidase (MAO). Phenelzine sulfate is a hydrazine derivative. It has a molecular weight of 234.27 and is chemically described as C8 H12 N2 • H2SO4. Its chemical structure is shown below:

Each NARDIL film-coated tablet for oral administration contains phenelzine sulfate equivalent to 15 mg of phenelzine base and the following inactive ingredients: mannitol, USP; croscarmellose sodium, NF; povidone, USP; edetate disodium, USP; magnesium stearate, NF; isopropyl alcohol, USP; purified water, USP; opadry orange Y30-13242A.

CLINICAL PHARMACOLOGY

Monoamine oxidase is a complex enzyme system, widely distributed throughout the body. Drugs that inhibit monoamine oxidase in the laboratory are associated with a number of clinical effects. Thus, it is unknown whether MAO inhibition per se, other pharmacologic actions, or an interaction of both is responsible for the clinical effects observed. Therefore, the physician should become familiar with all the effects produced by drugs of this class.

Pharmacokinetics

Absorption

Following a single 30 mg dose of NARDIL® (2 × 15 mg tablets), a mean peak plasma concentration (Cmax) of 19.8 ng/mL occurred at a time (Tmax) of 43 minutes postdose.

Metabolism

NARDIL® is extensively metabolized, primarily by oxidation via monoamine oxidase. After oral administration of ^13C6-phenelzine, 73% of the administered dose was recovered in urine as phenylacetic acid and parahydroxyphenylacetic acid within 96 hours. Acetylation to N^2-acetylphenelzine is a minor pathway.

Elimination

The mean elimination half-life after a single 30 mg dose is 11.6 hours. Multiple dose pharmacokinetics have not been studied in man.

INDICATIONS AND USAGE

NARDIL has been found to be effective in depressed patients clinically characterized as "atypical," "nonendogenous," or "neurotic." These patients often have mixed anxiety and depression and phobic or hypochondriacal features. There is less conclusive evidence of its usefulness with severely depressed patients with endogenous features.

NARDIL should rarely be the first antidepressant drug used. Rather, it is more suitable for use with patients who have failed to respond to the drugs more commonly used for these conditions.

CONTRAINDICATIONS

NARDIL should not be used in patients who are hypersensitive to the drug or its ingredients, with pheochromocytoma, congestive heart failure, severe renal impairment or renal disease, a history of liver disease, or abnormal liver function tests.

The potentiation of sympathomimetic substances and related compounds by MAO inhibitors may result in hypertensive crises (see WARNINGS). Therefore, patients being treated with NARDIL should not take sympathomimetic drugs (including amphetamines, cocaine, methylphenidate, dopamine, epinephrine, and norepinephrine) or related compounds (including methyldopa, L-dopa, L-tryptophan, L-tyrosine, and phenylalanine). Hypertensive crises during NARDIL therapy may also be caused by the ingestion of foods with a high concentration of tyramine or dopamine. Therefore, patients being treated with NARDIL should avoid high protein food that has undergone protein breakdown by aging, fermentation, pickling, smoking, or bacterial contamination. Patients should also avoid cheeses (especially aged varieties), pickled herring, beer, wine, liver, yeast extract (including brewer's yeast in large quantities), dry sausage (including Genoa salami, hard salami, pepperoni, and Lebanon bologna), pods of broad beans (fava beans), and yogurt. Excessive amounts of caffeine and chocolate may also cause hypertensive reactions.

NARDIL should not be used in combination with dextromethorphan or with CNS depressants such as alcohol and certain narcotics. Excitation, seizures, delirium, hyperpyrexia, circulatory collapse, coma, and death have been reported in patients receiving MAOI therapy who have been given a single dose of meperidine. NARDIL should not be administered together with or in rapid succession to other MAO inhibitors because HYPERTENSIVE CRISES and convulsive seizures, fever, marked sweating, excitation, delirium, tremor, coma, and circulatory collapse may occur.

Concomitant use with meperidine is contraindicated (see WARNINGS).

A List of MAO Inhibitors by Generic Name Follows:

pargyline hydrochloride
pargyline hydrochloride and methylclothiazide
furazolidone
isocarboxazid
procarbazine
tranylcypromine

NARDIL should also not be used in combination with buspirone HCl, since several cases of elevated blood pressure have been reported in patients taking MAO inhibitors who were then given buspirone HCl. At least 14 days should elapse between the discontinuation of NARDIL and the institution of another antidepressant or buspirone HCl, or the discontinuation of another MAO inhibitor and the institution of NARDIL.

There have been reports of serious reactions (including hyperthermia, rigidity, myoclonic movements and death) when serotoninergic drugs (e.g., dexfenfluramine, fluoxetine, fluvoxamine, paroxetine, sertraline, citalopram, venlafaxine) have been combined with an MAO inhibitor. Therefore, the concomitant use of NARDIL with serotoninergic agents is contraindicated (see PRECAUTIONS-Drug Interactions). At least 14 days should elapse between the discontinuation of an MAO inhibitor and the start of a serotonin re-uptake inhibitor or vice-versa, with the exception of fluoxetine. Allow at least five weeks between discontinuation of fluoxetine and initiation of NARDIL and at least 14 days between discontinuation of NARDIL and initiation of fluoxetine, or other serotoninergic agents. Before initiating NARDIL after using other serotoninergic agents, a sufficient amount of time must be allowed for clearance of the serotoninergic agent and its active metabolites.

The combination of MAO inhibitors and tryptophan has been reported to cause behavioral and neurologic syndromes including disorientation, confusion, amnesia, delirium, agitation, hypomanic signs, ataxia, myoclonus, hyperreflexia, shivering, ocular oscillations, and Babinski signs.

The concurrent administration of an MAO inhibitor and bupropion hydrochloride (Wellbutrin®) is contraindicated. At least 14 days should elapse between discontinuation of an MAO inhibitor and initiation of treatment with bupropion hydrochloride.

Patients taking NARDIL should not undergo elective surgery requiring general anesthesia. Also, they should not be given cocaine or local anesthesia containing sympathomimetic vasoconstrictors. The possible combined hypotensive effects of NARDIL and spinal anesthesia should be kept in mind. NARDIL should be discontinued at least 10 days prior to elective surgery.

MAO inhibitors, including NARDIL, are contraindicated in patients receiving guanethidine.

WARNINGS

Clinical Worsening and Suicide Risk

Patients with major depressive disorder (MDD), both adult and pediatric, may experience worsening of their depression and/or the emergence of suicidal ideation and behavior (suicidality) or unusual changes in behavior, whether or not they are taking antidepressant medications, and this risk may persist until significant remission occurs. Suicide is a known risk of depression and certain other psychiatric disorders, and these disorders themselves are the strongest predictors of suicide. There has been a long-standing concern, however, that antidepressants may have a role in inducing worsening of depression and the emergence of suicidality in certain patients during the early phases of treatment. Pooled analyses of short-term placebo-controlled trials of antidepressant drugs (SSRIs and others) showed that these drugs increase the risk of suicidal thinking and behavior (suicidality) in children, adolescents, and young adults (ages 18–24) with major depressive disorder (MDD) and other psychiatric disorders. Short-term studies did not show an increase in the risk of suicidality with antidepressants compared to placebo in adults beyond age 24; there was a reduction with antidepressants compared to placebo in adults aged 65 and older.

The pooled analyses of placebo-controlled trials in children and adolescents with MDD, obsessive compulsive disorder (OCD), or other psychiatric disorders included a total of 24 short-term trials of 9 antidepressant drugs in over 4400 patients. The pooled analyses of placebo-controlled trials in adults with MDD or other psychiatric disorders included a total of 295 short-term trials (median duration of 2 months) of 11 antidepressant drugs in over 77,000 patients. There was considerable variation in risk of suicidality among drugs, but a tendency toward an increase in the younger patients for almost all drugs studied. There were differences in absolute risk of suicidality across the different indications, with the highest incidence in MDD. The risk differences (drug vs placebo), however, were relatively stable within age strata and across indications. These risk differences (drug-placebo difference in the number of cases of suicidality per 1000 patients treated) are provided in Table 1.

Table 1
Age Range | Drug-Placebo Difference in Number of Cases of Suicidality per 1000 Patients Treated
 | Increases Compared to Placebo
<18 | 14 additional cases
18–24 | 5 additional cases
 | Decreases Compared to Placebo
25–64 | 1 fewer case
≥65 | 6 fewer cases

No suicides occurred in any of the pediatric trials. There were suicides in the adult trials, but the number was not sufficient to reach any conclusion about drug effect on suicide.

It is unknown whether the suicidality risk extends to longer-term use, i.e., beyond several months. However, there is substantial evidence from placebo-controlled maintenance trials in adults with depression that the use of antidepressants can delay the recurrence of depression.

All patients being treated with antidepressants for any indication should be monitored appropriately and observed closely for clinical worsening, suicidality, and unusual changes in behavior, especially during the initial few months of a course of drug therapy, or at times of dose changes, either increases or decreases.

The following symptoms, anxiety, agitation, panic attacks, insomnia, irritability, hostility, aggressiveness, impulsivity, akathisia (psychomotor restlessness), hypomania, and mania, have been reported in adult and pediatric patients being treated with antidepressants for major depressive disorder as well as for other indications, both psychiatric and nonpsychiatric. Although a causal link between the emergence of such symptoms and either the worsening of depression and/or the emergence of suicidal impulses has not been established, there is concern that such symptoms may represent precursors to emerging suicidality.

Consideration should be given to changing the therapeutic regimen, including possibly discontinuing the medication, in patients whose depression is persistently worse, or who are experiencing emergent suicidality or symptoms that might be precursors to worsening depression or suicidality, especially if these symptoms are severe, abrupt in onset, or were not part of the patient's presenting symptoms.

Families and caregivers of patients being treated with antidepressants for major depressive disorder or other indications, both psychiatric and nonpsychiatric, should be alerted about the need to monitor patients for the emergence of agitation, irritability, unusual changes in behavior, and the other symptoms described above, as well as the emergence of suicidality, and to report such symptoms immediately to health care providers. Such monitoring should include daily observation by families and caregivers. Prescriptions for Nardil should be written for the smallest quantity of tablets consistent with good patient management, in order to reduce the risk of overdose.

Screening Patients for Bipolar Disorder

A major depressive episode may be the initial presentation of bipolar disorder. It is generally believed (though not established in controlled trials) that treating such an episode with an antidepressant alone may increase the likelihood of precipitation of a mixed/manic episode in patients at risk for bipolar disorder. Whether any of the symptoms described above represent such a conversion is unknown. However, prior to initiating treatment with an antidepressant, patients with depressive symptoms should be adequately screened to determine if they are at risk for bipolar disorder; such screening should include a detailed psychiatric history, including a family history of suicide, bipolar disorder, and depression. It should be noted that Nardil is not approved for use in treating bipolar depression.

It should be noted that NARDIL is not approved for use in treating any indications in the pediatric population.

The most serious reactions to NARDIL involve changes in blood pressure.

Hypertensive Crises

The most important reaction associated with NARDIL administration is the occurrence of hypertensive crises, which have sometimes been fatal.

These crises are characterized by some or all of the following symptoms: occipital headache which may radiate frontally, palpitation, neck stiffness or soreness, nausea, vomiting, sweating (sometimes with fever and sometimes with cold, clammy skin), dilated pupils, and photophobia. Either tachycardia or bradycardia may be present and can be associated with constricting chest pain.

NOTE: Intracranial bleeding has been reported in association with the increase in blood pressure.

Blood pressure should be observed frequently to detect evidence of any pressor response in all patients receiving NARDIL. Therapy should be discontinued immediately upon the occurrence of palpitation or frequent headaches during therapy.

Recommended treatment in hypertensive crisis

If a hypertensive crisis occurs, NARDIL should be discontinued immediately and therapy to lower blood pressure should be instituted immediately. On the basis of present evidence, phentolamine is recommended. (The dosage reported for phentolamine is 5 mg intravenously.) Care should be taken to administer this drug slowly in order to avoid producing an excessive hypotensive effect. Fever should be managed by means of external cooling.

Warning to the Patient

All patients should be warned that the following foods, beverages, and medications must be avoided while taking NARDIL, and for two weeks after discontinuing use.

Foods and Beverages To Avoid

Meat and Fish
Pickled herring
Liver
Dry sausage (including Genoa salami, hard salami, pepperoni, and Lebanon bologna)

Vegetables
Broad bean pods (fava bean pods)
Sauerkraut

Dairy Products
Cheese (cottage cheese and cream cheese are allowed)
Yogurt

Beverages
Beer and wine
Alcohol-free and reduced-alcohol beer and wine products

Miscellaneous
Yeast extract (including brewer's yeast in large quantities)
Meat extract
Excessive amounts of chocolate and caffeine

Also, any spoiled or improperly refrigerated, handled, or stored protein-rich foods such as meats, fish, and dairy products, including foods that may have undergone protein changes by aging, pickling, fermentation, or smoking to improve flavor should be avoided.

OTC Medications To Avoid

Cold and cough preparations (including those containing dextromethorphan)
Nasal decongestants (tablets, drops, or spray)
Hay-fever medications
Sinus medications
Asthma inhalant medications
Antiappetite medicines
Weight-reducing preparations
"Pep" pills
L-tryptophan containing preparations

Also, certain prescription drugs should be avoided. Therefore, patients under the care of another physician or dentist should inform him/her that they are taking NARDIL.

Patients should be warned that the use of the above foods, beverages, or medications may cause a reaction characterized by headache and other serious symptoms due to a rise in blood pressure, with the exception of dextromethorphan which may cause reactions similar to those seen with meperidine. Also, there has been a report of an interaction between NARDIL and dextromethorphan (ingested as a lozenge) causing drowsiness and bizarre behavior.

Patients should be instructed to report promptly the occurrence of headache or other unusual symptoms.

Concomitant Use with Dibenzazepine Derivative Drugs

If the decision is made to administer NARDIL concurrently with other antidepressant drugs, or within less than 10 days after discontinuation of antidepressant therapy, the patient should be cautioned by the physician regarding the possibility of adverse drug interaction.

A List of Dibenzazepine Derivative Drugs by Generic Name Follows:

nortriptyline hydrochloride
amitriptyline hydrochloride
perphenazine and amitriptyline hydrochloride
clomipramine hydrochloride
desipramine hydrochloride
imipramine hydrochloride
doxepin
carbamazepine
cyclobenzaprine HCl
amoxapine
maprotiline HCl
trimipramine maleate
protriptyline HCl
mirtazapine

NARDIL should be used with caution in combination with antihypertensive drugs, including thiazide diuretics and β-blockers, since exaggerated hypotensive effects may result.

Use in Pregnancy

The safe use of NARDIL during pregnancy or lactation has not been established. The potential benefit of this drug, if used during pregnancy, lactation, or in women of childbearing age, should be weighed against the possible hazard to the mother or fetus.

Doses of NARDIL in pregnant mice well exceeding the maximum recommended human dose have caused a significant decrease in the number of viable offspring per mouse. In addition, the growth of young dogs and rats has been retarded by doses exceeding the maximum human dose.

PRECAUTIONS

Information for Patients

Prescribers or other health professionals should inform patients, their families, and their caregivers about the benefits and risks associated with treatment with Nardil and should counsel them in its appropriate use. A patient Medication Guide about "Antidepressant Medicines, Depression and other Serious Mental Illness, and Suicidal Thoughts or Actions" is available for Nardil. The prescriber or health professional should instruct patients, their families, and their caregivers to read the Medication Guide and should assist them in understanding its contents. Patients should be given the opportunity to discuss the contents of the Medication Guide and to obtain answers to any questions they may have. The complete text of the Medication Guide is reprinted at the end of this document.

Patients should be advised of the following issues and asked to alert their prescriber if these occur while taking Nardil.

Clinical Worsening and Suicide Risk

Patients, their families, and their caregivers should be encouraged to be alert to the emergence of anxiety, agitation, panic attacks, insomnia, irritability, hostility, aggressiveness, impulsivity, akathisia (psychomotor restlessness), hypomania, mania, other unusual changes in behavior, worsening of depression, and suicidal ideation, especially early during antidepressant treatment and when the dose is adjusted up or down. Families and caregivers of patients should be advised to look for the emergence of such symptoms on a day-to-day basis, since changes may be abrupt. Such symptoms should be reported to the patient's prescriber or health professional, especially if they are severe, abrupt in onset, or were not part of the patient's presenting symptoms. Symptoms such as these may be associated with an increased risk for suicidal thinking and behavior and indicate a need for very close monitoring and possibly changes in the medication.

Pediatric Use

Safety and effectiveness in the pediatric population have not been established (see BOX WARNING and WARNINGS—Clinical Worsening and Suicide Risk).

Anyone considering the use of NARDIL in a child or adolescent must balance the potential risks with the clinical need.

Nardil, as with other hydrazine derivatives, has been reported to induce pulmonary and vascular tumors in an uncontrolled lifetime study in mice.

In depressed patients, the possibility of suicide should always be considered and adequate precautions taken. It is recommended that careful observations of patients undergoing NARDIL treatment be maintained until control of depression is achieved. If necessary, additional measures (ECT, hospitalization, etc) should be instituted.

All patients undergoing treatment with NARDIL should be closely followed for symptoms of postural hypotension. Hypotensive side effects have occurred in hypertensive as well as normotensive and hypotensive patients. Blood pressure usually returns to pretreatment levels rapidly when the drug is discontinued or the dosage is reduced.

Because the effect of NARDIL on the convulsive threshold may be variable, adequate precautions should be taken when treating epileptic patients.

Of the more severe side effects that have been reported with any consistency, hypomania has been the most common. This reaction has been largely limited to patients in whom disorders characterized by hyperkinetic symptoms coexist with, but are obscured by, depressive affect; hypomania usually appeared as depression improved. If agitation is present, it may be increased with NARDIL. Hypomania and agitation have also been reported at higher than recommended doses or following long-term therapy.

NARDIL may cause excessive stimulation in schizophrenic patients; in manic-depressive states it may result in a swing from a depressive to a manic phase.

NARDIL should be used with caution in diabetes mellitus; increased insulin sensitivity may occur. Requirements for insulin or oral hypoglycemics may be decreased.

MAO inhibitors, including NARDIL, potentiate hexobarbital hypnosis in animals. Therefore, barbiturates should be given at a reduced dose with NARDIL.

MAO inhibitors inhibit the destruction of serotonin and norepinephrine, which are believed to be released from tissue stores by rauwolfia alkaloids. Accordingly, caution should be exercised when rauwolfia is used concomitantly with an MAO inhibitor, including NARDIL.

There is conflicting evidence as to whether or not MAO inhibitors affect glucose metabolism or potentiate hypoglycemic agents. This should be kept in mind if NARDIL is administered to diabetics.

Drug Interactions

In patients receiving nonselective monoamine oxidase (MAO) inhibitors in combination with serotoninergic agents (e.g., dexfenfluramine, fluoxetine, fluvoxamine, paroxetine, sertraline, citalopram, venlafaxine) there have been reports of serious, sometimes fatal, reactions. Because NARDIL is a monoamine oxidase (MAO) inhibitor, NARDIL should not be used concomitantly with a serotoninergic agent (See CONTRAINDICATIONS).

Administration of guanethidine to patients receiving an MAO inhibitor can produce moderate to severe hypertension due to release of catecholamines. At least two weeks should elapse between withdrawal of the MAO inhibitor and the initiation of guanethidine. (see CONTRAINDICATIONS)

Geriatric Use

Clinical studies of NARDIL did not include sufficient numbers of subjects aged 65 and over to determine whether they respond differently from younger subjects. Other reported clinical experience has not identified differences in responses between the elderly and younger patients. In general, dose selection for an elderly patient should be cautious, usually starting at the low end of the dosing range, reflecting the greater frequency of decreased hepatic, renal, or cardiac function, and of concomitant disease or other drug therapy.

ADVERSE REACTIONS

NARDIL is a potent inhibitor of monoamine oxidase. Because this enzyme is widely distributed throughout the body, diverse pharmacologic effects can be expected to occur. When they occur, such effects tend to be mild or moderate in severity (see below), often subside as treatment continues, and can be minimized by adjusting dosage; rarely is it necessary to institute counteracting measures or to discontinue NARDIL.

Common side effects include:

Nervous System—Dizziness, headache, drowsiness, sleep disturbances (including insomnia and hypersomnia), fatigue, weakness, tremors, twitching, myoclonic movements, hyperreflexia.

Gastrointestinal—Constipation, dry mouth, gastrointestinal disturbances, elevated serum transaminases (without accompanying signs and symptoms).

Metabolic—Weight gain.

Cardiovascular—Postural hypotension, edema.

Genitourinary—Sexual disturbances, eg, anorgasmia and ejaculatory disturbances and impotence.

Less common mild to moderate side effects (some of which have been reported in a single patient or by a single physician) include:

Nervous System—Jitteriness, palilalia, euphoria, nystagmus, paresthesias.

Genitourinary—Urinary retention.

Metabolic—Hypernatremia.

Dermatologic—Pruritus, skin rash, sweating.

Special Senses—Blurred vision, glaucoma.

Although reported less frequently, and sometimes only once, additional severe side effects include:

Nervous System—Ataxia, shock-like coma, toxic delirium, manic reaction, convulsions, acute anxiety reaction, precipitation of schizophrenia, transient respiratory and cardiovascular depression following ECT.

Gastrointestinal—To date, fatal progressive necrotizing hepatocellular damage has been reported in very few patients. Reversible jaundice.

Hematologic—Leukopenia.

Immunologic—Lupus-like syndrome

Metabolic—Hypermetabolic syndrome (which may include, but is not limited to, hyperpyrexia, tachycardia, tachypnea, muscular rigidity, elevated CK levels, metabolic acidosis, hypoxia, coma and may resemble an overdose).

Respiratory—Edema of the glottis.

General—Fever associated with increased muscle tone.

Withdrawal may be associated with nausea, vomiting, and malaise.

An uncommon withdrawal syndrome following abrupt withdrawal of NARDIL has been infrequently reported. Signs and symptoms of this syndrome generally commence 24 to 72 hours after drug discontinuation and may range from vivid nightmares with agitation to frank psychosis and convulsions. This syndrome generally responds to reinstitution of low-dose NARDIL therapy followed by cautious downward titration and discontinuation.

DOSAGE AND ADMINISTRATION

Initial dose

The usual starting dose of NARDIL is one tablet (15 mg) three times a day.

Early phase treatment

Dosage should be increased to at least 60 mg per day at a fairly rapid pace consistent with patient tolerance. It may be necessary to increase dosage up to 90 mg per day to obtain sufficient MAO inhibition. Many patients do not show a clinical response until treatment at 60 mg has been continued for at least 4 weeks.

Maintenance dose

After maximum benefit from NARDIL is achieved, dosage should be reduced slowly over several weeks. Maintenance dose may be as low as one tablet, 15 mg, a day or every other day, and should be continued for as long as is required.

OVERDOSAGE

Note—For management of hypertensive crises see WARNINGS section.

Accidental or intentional overdosage may be more common in patients who are depressed. It should be remembered that multiple drugs and/or alcohol may have been ingested.

Depending on the amount of overdosage with NARDIL, a varying and mixed clinical picture may develop, including signs and symptoms of central nervous system and cardiovascular stimulation and/or depression. Signs and symptoms may be absent or minimal during the initial 12-hour period following ingestion and may develop slowly thereafter, reaching a maximum in 24–48 hours. Death has been reported following overdosage. Therefore, immediate hospitalization, with continuous patient observation and monitoring throughout this period, is essential.

Signs and symptoms of overdosage may include, alone or in combination, any of the following: drowsiness, dizziness, faintness, irritability, hyperactivity, agitation, severe headache, hallucinations, trismus, opisthotonus, rigidity, convulsions, and coma; rapid and irregular pulse, hypertension, hypotension, and vascular collapse; precordial pain, respiratory depression and failure, hyperpyrexia, diaphoresis, and cool, clammy skin.

Treatment

Intensive symptomatic and supportive treatment may be required. Induction of emesis or gastric lavage with instillation of charcoal slurry may be helpful in early poisoning, provided the airway has been protected against aspiration. Signs and symptoms of central nervous system stimulation, including convulsions, should be treated with diazepam, given slowly intravenously. Phenothiazine derivatives and central nervous system stimulants should be avoided. Hypotension and vascular collapse should be treated with intravenous fluids and, if necessary, blood pressure titration with an intravenous infusion of dilute pressor agent. It should be noted that adrenergic agents may produce a markedly increased pressor response.

Respiration should be supported by appropriate measures, including management of the airway, use of supplemental oxygen, and mechanical ventilatory assistance, as required.

Body temperature should be monitored closely. Intensive management of hyperpyrexia may be required. Maintenance of fluid and electrolyte balance is essential.

There are no data on the lethal dose in man. The pathophysiologic effects of massive overdosage may persist for several days, since the drug acts by inhibiting physiologic enzyme systems. With symptomatic and supportive measures, recovery from mild overdosage may be expected within 3 to 4 days.

Hemodialysis, peritoneal dialysis, and charcoal hemoperfusion may be of value in massive overdosage, but sufficient data are not available to recommend their routine use in these cases.

Toxic blood levels of phenelzine have not been established, and assay methods are not practical for clinical or toxicological use.

HOW SUPPLIED

Each NARDIL tablet is orange, biconvex, film-coated, and engraved with "P-D 270" and contains phenelzine sulfate equivalent to 15 mg of phenelzine base.

NDC 0071-0350-60. Bottle of 60

Storage

Store between 15° – 30°C (59° – 86°F).

Rx only

LAB-0201-12.0

Revised February 2009

Medication Guide Antidepressant Medicines, Depression and other Serious Mental Illnesses, and Suicidal Thoughts or Actions

Read the Medication Guide that comes with you or your family member's antidepressant medicine. This Medication Guide is only about the risk of suicidal thoughts and actions with antidepressant medicines. Talk to your, or your family member's, healthcare provider about:

- all risks and benefits of treatment with antidepressant medicines
- all treatment choices for depression or other serious mental illness

What is the most important information I should know about antidepressant medicines, depression and other serious mental illnesses, and suicidal thoughts or actions?

1. Antidepressant medicines may increase suicidal thoughts or actions in some children, teenagers, and young adults within the first few months of treatment.
2. Depression and other serious mental illnesses are the most important causes of suicidal thoughts and actions. Some people may have a particularly high risk of having suicidal thoughts or actions. These include people who have (or have a family history of) bipolar illness (also called manic-depressive illness) or suicidal thoughts or actions.
3. How can I watch for and try to prevent suicidal thoughts and actions in myself or a family member?
  1. Pay close attention to any changes, especially sudden changes, in mood, behaviors, thoughts, or feelings. This is very important when an antidepressant medicine is started or when the dose is changed.
  2. Call the healthcare provider right away to report new or sudden changes in mood, behavior, thoughts, or feelings.
  3. Keep all follow-up visits with the healthcare provider as scheduled. Call the healthcare provider between visits as needed, especially if you have concerns about symptoms.

Call a healthcare provider right away if you or your family member has any of the following symptoms, especially if they are new, worse, or worry you:

- thoughts about suicide or dying
- attempts to commit suicide
- new or worse depression
- new or worse anxiety
- feeling very agitated or restless
- panic attacks
- an extreme increase in activity and talking (mania)
- trouble sleeping (insomnia)
- new or worse irritability
- acting aggressive, being angry, or violent
- acting on dangerous impulses
- other unusual changes in behavior or mood

Call your doctor for medical advice about side effects. You may report side effects to FDA at 1-800-FDA-1088.

What else do I need to know about antidepressant medicines?

- Never stop an antidepressant medicine without first talking to a healthcare provider. Stopping an antidepressant medicine suddenly can cause other symptoms.
- Antidepressants are medicines used to treat depression and other illnesses. It is important to discuss all the risks of treating depression and also the risks of not treating it. Patients and their families or other caregivers should discuss all treatment choices with the healthcare provider, not just the use of antidepressants.
- Antidepressant medicines have other side effects. Talk to the healthcare provider about the side effects of the medicine prescribed for you or your family member.
- Antidepressant medicines can interact with other medicines. Know all of the medicines that you or your family member takes. Keep a list of all medicines to show the healthcare provider. Do not start new medicines without first checking with your healthcare provider.
- Not all antidepressant medicines prescribed for children are FDA approved for use in children. Talk to your child's healthcare provider for more information.

This Medication Guide has been approved by the U.S. Food and Drug Administration for all antidepressants.

Revised October 2008

PRINCIPAL DISPLAY PANEL - 15 mg Tablet Bottle Label

ALWAYS DISPENSE WITH MEDICATION GUIDE

Pfizer

NDC 0071-0350-60

Nardil®
(phenelzine sulfate
tablets, USP)

15 mg*

60 Tablets
Rx only